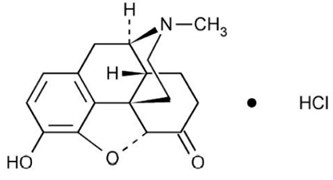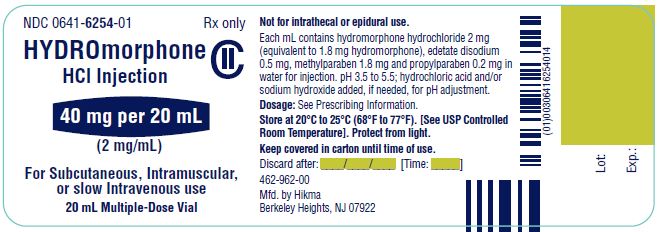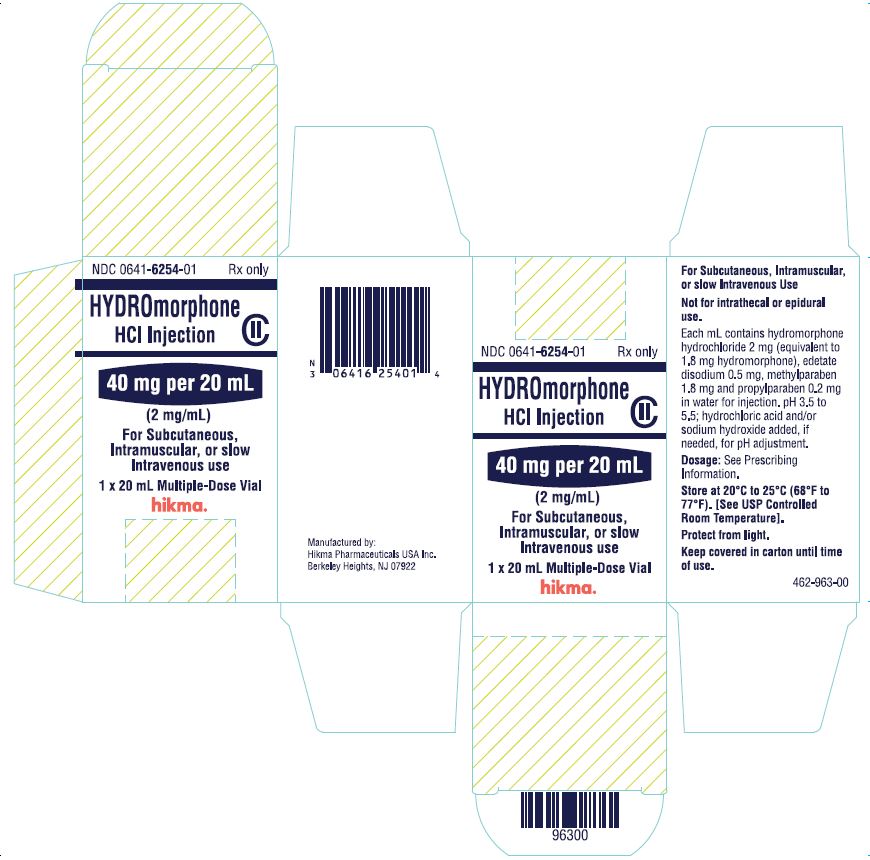 DRUG LABEL: Hydromorphone Hydrochloride
NDC: 0641-6254 | Form: INJECTION, SOLUTION
Manufacturer: Hikma Pharmaceuticals USA Inc.
Category: prescription | Type: HUMAN PRESCRIPTION DRUG LABEL
Date: 20231215
DEA Schedule: CII

ACTIVE INGREDIENTS: HYDROMORPHONE HYDROCHLORIDE 2 mg/1 mL
INACTIVE INGREDIENTS: EDETATE DISODIUM 0.5 mg/1 mL; METHYLPARABEN 1.8 mg/1 mL; PROPYLPARABEN 0.2 mg/1 mL; WATER; SODIUM HYDROXIDE; HYDROCHLORIC ACID

HIGHLIGHTS OF PRESCRIBING INFORMATION

These highlights do not include all the information needed to use HYDROMORPHONE HYDROCHLORIDE INJECTION safely and effectively. See full prescribing information for HYDROMORPHONE HYDROCHLORIDE INJECTION.
HYDROMORPHONE HYDROCHLORIDE INJECTION, for intravenous, intramuscular, or subcutaneous use, CII
Initial U.S. Approval: January 1984

WARNING: SERIOUS AND LIFE-THREATENING RISKS FROM USE OF HYDROMORPHONE HYDROCHLORIDE INJECTION

See full prescribing information for complete boxed warning.

- Hydromorphone Hydrochloride Injection exposes users to risks of addiction, abuse, and misuse, which can lead to overdose and death. Assess patient’s risk before prescribing and monitor regularly for these behaviors and conditions. (5.1)
- Serious, life-threatening, or fatal respiratory depression may occur. Monitor closely, especially upon initiation or following a dosage increase. To reduce the risk of respiratory depression, proper dosing and titration of Hydromorphone Hydrochloride Injection are essential. (5.2)
- Concomitant use of opioids with benzodiazepines or other central nervous system (CNS) depressants, including alcohol, may result in profound sedation, respiratory depression, coma, and death. Reserve concomitant prescribing for use in patients for whom alternative treatment options are inadequate. (5.3, 7)
- If opioid use is required for an extended period of time in a pregnant woman, advise the patient of the risk of Neonatal Opioid Withdrawal Syndrome, which may be life-threatening if not recognized and treated. Ensure that management by neonatology experts will be available at delivery. (5.4)

1 INDICATIONS AND USAGE

Hydromorphone Hydrochloride Injection is an opioid agonist indicated for the management of pain severe enough to require an opioid analgesic and for which alternate treatments are inadequate. (1)

Limitations of Use: (1)

Because of the risks of addiction, abuse, and misuse with opioids, which can occur at any dosage or duration (5.1), reserve Hydromorphone Hydrochloride Injection for use in patients for whom alternative treatment options (e.g., non-opioid analgesics or opioid combination products):

- Have not been tolerated, or are not expected to be tolerated
- Have not provided adequate analgesia or are not expected to provide adequate analgesia

Hydromorphone Hydrochloride Injection should not be used for an extended period of time unless the pain remains severe enough to require an opioid analgesic and for which alternative treatment options continue to be inadequate.

2 DOSAGE AND ADMINISTRATION

- Hydromorphone Hydrochloride Injection should be prescribed only by healthcare professionals who are knowledgeable about the use of opioids and how to mitigate the associated risks. (2.1)

- Use the lowest effective dosage for the shortest duration consistent with individual patient treatment goals. Reserve titration to higher doses of Hydromorphone Hydrochloride Injection for patients in whom lower doses are insufficiently effective and in whom the expected benefits of using a higher dose opioid clearly outweigh the substantial risks. (2.1, 5)
- Many acute pain conditions (e.g., the pain that occurs with a number of surgical procedures or acute musculoskeletal injuries) require no more than a few days of an opioid analgesic. Clinical guidelines on opioid prescribing for some acute pain conditions are available. (2.1)
- Initiate the dosing regimen for each patient individually, taking into account the patient’s underlying cause and severity of pain, prior analgesic treatment and response, and risk factors for addiction, abuse, and misuse. (2.1, 5.1)

- Respiratory depression can occur at any time during opioid therapy, especially when initiating and following dosage increases with Hydromorphone Hydrochloride Injection. Consider this risk when selecting an initial dose and when making dose adjustments. (2.1, 5.2)
- Initial Dosage:
  - Intramuscular or Subcutaneous Use: The usual starting dose is 1 mg to 2 mg every 2 to 3 hours as necessary. (2.2)
  - Intravenous Use: The usual starting dose is 0.2 mg to 1 mg every 2 to 3 hours. The injection should be given slowly, over at least 2 to 3 minutes. (2.2)
- Hepatic Impairment: Initiate treatment with one-fourth to one-half the usual starting dose, depending on degree of hepatic impairment. (2.3)
- Renal Impairment: Initiate treatment with one-fourth to one-half the usual starting dose, depending on degree of renal impairment. (2.4)
- Do not abruptly discontinue Hydromorphone Hydrochloride Injection in a physically-dependent patient. (2.6, 5.12)

3 DOSAGE FORMS AND STRENGTHS

Injection: 40 mg/20 mL (2 mg/mL) hydromorphone hydrochloride in a multiple-dose vial. (3)

4 CONTRAINDICATIONS

- Significant respiratory depression. (4)
- Acute or severe bronchial asthma in an unmonitored setting or in absence of resuscitative equipment. (4)
- Known or suspected gastrointestinal obstruction, including paralytic ileus. (4)
- Known hypersensitivity to hydromorphone, hydromorphone salts, or any other components of the product. (4)

5 WARNINGS AND PRECAUTIONS

- Opioid-Induced Hyperalgesia and Allodynia: Opioid-Induced ‎Hyperalgesia (OIH) occurs when an opioid analgesic ‎paradoxically causes an ‎increase in pain, or an increase in ‎sensitivity to pain. If OIH is suspected, carefully consider appropriately decreasing the dose of the current opioid analgesic or opioid rotation. (5.5)
- Life-Threatening Respiratory Depression in Patients with Chronic Pulmonary Disease or in Elderly, Cachectic, or Debilitated Patients: Monitor closely, particularly during initiation and titration. (5.6)
- Adrenal Insufficiency: If diagnosed, treat with physiologic replacement of corticosteroids, and wean patient off of the opioid. (5.7)
- Severe Hypotension: Monitor during dosage initiation and titration. Avoid use of Hydromorphone Hydrochloride Injection in patients with circulatory shock. (5.8)
- Risks of Use in Patients with Increased Intracranial Pressure, Brain Tumors, Head Injury, or Impaired Consciousness: Monitor for sedation and respiratory depression. Avoid use of Hydromorphone Hydrochloride Injection in patients with impaired consciousness or coma. (5.9)

6 ADVERSE REACTIONS

Most common adverse reactions are lightheadedness, dizziness, sedation, nausea, vomiting, sweating, flushing, dysphoria, euphoria, dry mouth, and pruritus. (6)

To report Suspected Adverse Reactions, contact Hikma Pharmaceuticals USA Inc. at 1-877-845-0689 or FDA at 1-800-FDA-1088 or www.fda.gov/medwatch.

7 DRUG INTERACTIONS

- Serotonergic Drugs: Concomitant use may result in serotonin syndrome. Discontinue Hydromorphone Hydrochloride Injection if serotonin syndrome is suspected. (7)
- Monoamine Oxidase Inhibitors (MAOIs): Can potentiate the effects of hydromorphone. Avoid concomitant use in patients receiving MAOIs or within 14 days of stopping treatment with an MAOI. (7)
- Mixed Agonist/Antagonist and Partial Agonist Opioid Analgesics: Avoid use with Hydromorphone Hydrochloride Injection because they may reduce analgesic effect of Hydromorphone Hydrochloride Injection or precipitate withdrawal symptoms. (7)

8 USE IN SPECIFIC POPULATIONS

- Pregnancy: May cause fetal harm. (8.1)

FULL PRESCRIBING INFORMATION

WARNING: SERIOUS AND LIFE-THREATENING RISKS FROM USE OF HYDROMORPHONE HYDROCHLORIDE INJECTION

Addiction, Abuse, and Misuse

Because the use of Hydromorphone Hydrochloride Injection exposes patients and other users to the risks of opioid addiction, abuse, and misuse, which can lead to overdose and death, assess each patient’s risk prior to prescribing and reassess all patients regularly for the development of these behaviors and conditions [see Warnings and Precautions (5.1)].

Life-Threatening Respiratory Depression

Serious, life-threatening, or fatal respiratory depression may occur with use of Hydromorphone Hydrochloride Injection, especially during initiation or following a dosage increase. To reduce the risk of respiratory depression, proper dosing and titration of Hydromorphone Hydrochloride Injection are essential [see Warnings and Precautions (5.2)].

Risks From Concomitant Use With Benzodiazepines Or Other CNS Depressants

Concomitant use of opioids with benzodiazepines or other central nervous system (CNS) depressants, including alcohol, may result in profound sedation, respiratory depression, coma, and death. Reserve concomitant prescribing of Hydromorphone Hydrochloride Injection and benzodiazepines or other CNS depressants for use in patients for whom alternative treatment options are inadequate [see Warnings and Precautions (5.3), Drug Interactions (7)].

Neonatal Opioid Withdrawal Syndrome (NOWS)

If opioid use is required for an extended period of time in a pregnant woman, advise the patient of the risk of NOWS, which may be life-threatening if not recognized and treated. Ensure that management by neonatology experts will be available at delivery [see Warnings and Precautions (5.4)].

1 INDICATIONS AND USAGE

Hydromorphone Hydrochloride Injection is indicated for the management of pain severe enough to require an opioid analgesic and for which alternative treatments are inadequate.

Limitations of Use

Because of the risks of addiction, abuse, and misuse with opioids, which can occur at any dosage or duration [see Warnings and Precautions (5.1)], reserve Hydromorphone Hydrochloride Injection for use in patients for whom alternative treatment options (e.g., non-opioid analgesics or opioid combination products):

- Have not been tolerated or are not expected to be tolerated
- Have not provided adequate analgesia or are not expected to provide adequate analgesia

Hydromorphone Hydrochloride Injection should not be used for an extended period of time unless the pain remains severe enough to require an opioid analgesic and for which alternative treatment options continue to be inadequate.

2 DOSAGE AND ADMINISTRATION

2.1 Important Dosage and Administration Instructions

- Hydromorphone Hydrochloride Injection should be prescribed only by healthcare professionals who are knowledgeable about the use of opioids and how to mitigate the associated risks.
- Use the lowest effective dosage for the shortest duration of time consistent with individual patient treatment goals [see Warnings and Precautions (5)]. Because the risk of overdose increases as opioid doses increase, reserve titration to higher doses of Hydromorphone Hydrochloride Injection for patients in whom lower doses are insufficiently effective and in whom the expected benefits of using a higher dose opioid clearly outweigh the substantial risks.
- Many acute pain conditions (e.g., the pain that occurs with a number of surgical procedures or acute musculoskeletal injuries) require no more than a few days of an opioid analgesic. Clinical guidelines on opioid prescribing for some acute pain conditions are available.
- There is variability in the opioid analgesic dose and duration needed to adequately manage pain due both to the cause of pain and to individual patient factors. Initiate the dosing regimen for each patient individually, taking into account the patient’s underlying cause and severity of pain, prior analgesic treatment and response, and risk factors for addiction, abuse, and misuse [see Warnings and Precautions (5.1)].
- Respiratory depression can occur at any time during opioid therapy, especially when initiating and following dosage increases with Hydromorphone Hydrochloride Injection. Consider this risk when selecting an initial dose and when making dose adjustments [see Warnings and Precautions (5.2)].
- Inspect Hydromorphone Hydrochloride Injection for particulate matter and discoloration prior to administration. A 0.2 mg/mL admixture of Hydromorphone Hydrochloride Injection in 0.9% sodium chloride or 5% dextrose is physically compatible and chemically stable for 24 hours at 25°C, protected from light.
- Use or discard multi-dose vials within 28 days of the first use.

2.2 Initial Dosage

Use of Hydromorphone Hydrochloride Injection as the First Opioid Analgesic

Subcutaneous or Intramuscular Administration:
Initiate treatment with Hydromorphone Hydrochloride Injection in a dosing range of 1 mg to 2 mg every 2 to 3 hours as needed for pain, and the lowest dose necessary to achieve adequate analgesia. Titrate the dose based upon the individual patient’s response to their initial dose of Hydromorphone Hydrochloride Injection.

Intravenous Administration:
The initial starting dose is 0.2 mg to 1 mg every 2 to 3 hours. Intravenous administration should be given slowly, over at least 2 to 3 minutes, depending on the dose. The initial dose should be reduced in the elderly or debilitated and may be lowered to 0.2 mg.

Conversion from Other Opioids to Hydromorphone Hydrochloride Injection

There is inter-patient variability in the potency of opioid drugs and opioid formulations. Therefore, a conservative approach is advised when determining the total daily dosage of Hydromorphone Hydrochloride Injection. It is safer to underestimate a patient’s 24-hour Hydromorphone Hydrochloride Injection dosage than to overestimate the 24-hour Hydromorphone Hydrochloride Injection dosage and manage an adverse reaction due to overdose.

If the decision is made to convert to Hydromorphone Hydrochloride Injection from another opioid analgesic using publicly available data, convert the current total daily amount(s) of opioid(s) received to an equivalent total daily dose of Hydromorphone Hydrochloride Injection and reduce by one-half due to the possibility of incomplete cross tolerance. Divide the new total amount by the number of doses permitted based on dosing interval (e.g., 8 doses for every-three-hour dosing). Titrate the dose according to the patient's response.

2.3 Dosage Modifications in Patients with Hepatic Impairment

Start patients with hepatic impairment on one-fourth to one-half the usual Hydromorphone Hydrochloride Injection starting dose depending on the extent of impairment [see Clinical Pharmacology (12.3)].

2.4 Dosage Modifications in Patients with Renal Impairment

Start patients with renal impairment on one-fourth to one-half the usual Hydromorphone Hydrochloride Injection starting dose depending on the degree of impairment [see Clinical Pharmacology (12.3)].

2.5 Titration and Maintenance of Therapy

Titrate the dose based upon the individual patient’s response to their initial dose of Hydromorphone Hydrochloride Injection. Individually titrate Hydromorphone Hydrochloride Injection to a dose that provides adequate analgesia and minimizes adverse reactions. Continually reevaluate patients receiving Hydromorphone Hydrochloride Injection to assess the maintenance of pain control, signs and symptoms of opioid withdrawal, and other adverse reactions, as well as to reassess for the development of addiction, abuse, or misuse [see Warnings and Precautions (5.1, 5.12)]. Frequent communication is important among the prescriber, other members of the healthcare team, the patient, and the caregiver/family during periods of changing analgesic requirements, including initial titration.

If the level of pain increases after dosage stabilization, attempt to identify the source of increased pain before increasing the Hydromorphone Hydrochloride Injection dosage. If after increasing the dosage, unacceptable opioid-related adverse reactions are observed (including an increase in pain after a dosage increase), consider reducing the dosage [see Warnings and Precautions (5)]. Adjust the dosage to obtain an appropriate balance between management of pain and opioid-related adverse reactions.

2.6 Safe Reduction or Discontinuation of Hydromorphone Hydrochloride Injection

When a patient who has been taking Hydromorphone Hydrochloride Injection regularly and may be physically dependent no longer requires therapy with Hydromorphone Hydrochloride Injection, taper the dose gradually, by 25% to 50% every 2 to 4 days, while monitoring carefully for signs and symptoms of withdrawal. If the patient develops these signs or symptoms, raise the dose to the previous level and taper more slowly, either by increasing the interval between decreases, decreasing the amount of change in dose, or both. Do not abruptly discontinue Hydromorphone Hydrochloride Injection in a physically-dependent patient [see Warnings and Precautions (5.12), Drug Abuse and Dependence (9.3)].

3 DOSAGE FORMS AND STRENGTHS

Injection: 40 mg/20 mL (2 mg/mL) hydromorphone hydrochloride is available as a sterile, clear, colorless liquid solution in a multiple-dose vial.

4 CONTRAINDICATIONS

Hydromorphone Hydrochloride Injection is contraindicated in patients with:

• Significant respiratory depression [see Warnings and Precautions (5.2)]

• Acute or severe bronchial asthma in an unmonitored setting or in the absence of resuscitative equipment [see Warnings and Precautions (5.2)]

• Known or suspected gastrointestinal obstruction, including paralytic ileus [see Warnings and Precautions (5.10)]

• Hypersensitivity to hydromorphone, hydromorphone salts, any other components of the product.

5 WARNINGS AND PRECAUTIONS

5.1 Addiction, Abuse, and Misuse

Hydromorphone Hydrochloride Injection contains hydromorphone, a Schedule II controlled substance. As an opioid, Hydromorphone Hydrochloride Injection exposes users to the risks of addiction, abuse, and misuse [see Drug Abuse and Dependence (9)].

Although the risk of addiction in any individual is unknown, it can occur in patients appropriately prescribed Hydromorphone Hydrochloride Injection. Addiction can occur at recommended dosages and if the drug is misused or abused.

Assess each patient’s risk for opioid addiction, abuse, or misuse prior to prescribing Hydromorphone Hydrochloride Injection and monitor all patients receiving Hydromorphone Hydrochloride Injection for the development of these behaviors and conditions. Risks are increased in patients with a personal or family history of substance abuse (including drug or alcohol abuse or addiction) or mental illness (e.g., major depression). The potential for these risks should not, however, prevent the proper management of pain in any given patient. Patients at increased risk may be prescribed opioids such as Hydromorphone Hydrochloride Injection but use in such patients necessitates intensive counseling about the risks and proper use of Hydromorphone Hydrochloride Injection along with intensive monitoring for signs of addiction, abuse, and misuse.

Opioids are sought for nonmedical use and are subject to diversion from legitimate prescribed use. Consider these risks when prescribing or dispensing Hydromorphone Hydrochloride Injection. Strategies to reduce these risks include prescribing the drug in the smallest appropriate quantity.

Contact local state professional licensing board or state-controlled substances authority for information on how to prevent and detect abuse or diversion of this product.

5.2 Life-Threatening Respiratory Depression

Serious, life-threatening, or fatal respiratory depression has been reported with the use of opioids, even when used as recommended. Respiratory depression, if not immediately recognized and treated, may lead to respiratory arrest and death. Management of respiratory depression may include close observation, supportive measures, and use of opioid antagonists, depending on the patient’s clinical status [see Overdosage (10)]. Carbon dioxide (CO2) retention from opioid-induced respiratory depression can exacerbate the sedating effects of opioids.

While serious, life-threatening, or fatal respiratory depression can occur at any time during the use of Hydromorphone Hydrochloride Injection, the risk is greatest during the initiation of therapy or following a dosage increase.

To reduce the risk of respiratory depression, proper dosing and titration of Hydromorphone Hydrochloride Injection are essential [see Dosage and Administration (2)]. Overestimating the Hydromorphone Hydrochloride Injection dosage when converting patients from another opioid product can result in a fatal overdose with the first dose.

Opioids can cause sleep-related breathing disorders including central sleep apnea (CSA) and sleep-related hypoxemia. Opioid use increases the risk of CSA in a dose-dependent fashion. In patients who present with CSA, consider decreasing the opioid dosage using best practices for opioid taper [see Dosage and Administration (2.6)].

5.3 Risks from Concomitant Use with Benzodiazepines or Other CNS Depressants

Profound sedation, respiratory depression, coma, and death may result from the concomitant use of Hydromorphone Hydrochloride Injection with benzodiazepines and/or other CNS depressants, including alcohol (e.g., non-benzodiazepine sedatives/hypnotics, anxiolytics, tranquilizers, muscle relaxants, general anesthetics, antipsychotics, other opioids). Because of these risks, reserve concomitant prescribing of these drugs for use in patients for whom alternative treatment options are inadequate.

Observational studies have demonstrated that concomitant use of opioid analgesics and benzodiazepines increases the risk of drug-related mortality compared to use of opioid analgesics alone. Because of similar pharmacological properties, it is reasonable to expect similar risk with the concomitant use of other CNS depressant drugs with opioid analgesics [see Drug Interactions (7)].

If the decision is made to prescribe a benzodiazepine or other CNS depressant concomitantly with an opioid analgesic, prescribe the lowest effective dosages and minimum durations of concomitant use. In patients already receiving an opioid analgesic, prescribe a lower initial dose of the benzodiazepine or other CNS depressant than indicated in the absence of an opioid, and titrate based on clinical response. If an opioid analgesic is initiated in a patient already taking a benzodiazepine or other CNS depressant, prescribe a lower initial dose of the opioid analgesic, and titrate based on clinical response. Monitor patients closely for signs and symptoms of respiratory depression and sedation.

5.4 Neonatal Opioid Withdrawal Syndrome

Use of Hydromorphone Hydrochloride Injection for an extended period of time during pregnancy can result in withdrawal in the neonate. Neonatal opioid withdrawal syndrome, unlike opioid withdrawal syndrome in adults, may be life-threatening if not recognized and treated, and requires management according to protocols developed by neonatology experts. Observe newborns for signs of neonatal opioid withdrawal syndrome and manage accordingly. Advise pregnant women using opioids for an extended period of time of the risk of neonatal opioid withdrawal syndrome and ensure that management by neonatology experts will be available at delivery [see Use in Specific Populations (8.1)].

5.5 Opioid-Induced Hyperalgesia and Allodynia

Opioid-Induced Hyperalgesia (OIH) occurs when an opioid analgesic paradoxically causes an increase in pain, or an increase in sensitivity to pain. This condition differs from tolerance, which is the need for increasing doses of opioids to maintain a defined effect [see Drug Abuse and Dependence (9.3)]. Symptoms of OIH include (but may not be limited to) increased levels of pain upon opioid dosage increase, decreased levels of pain upon opioid dosage decrease, or pain from ordinarily non-painful stimuli (allodynia). These
symptoms may suggest OIH only if there is no evidence of underlying disease progression, opioid tolerance, opioid withdrawal, or addictive behavior.

Cases of OIH have been reported, both with short-term and longer-term use of opioid analgesics. Though the mechanism of OIH is not fully understood, multiple
biochemical pathways have been implicated. Medical literature suggests a strong biologic plausibility between opioid analgesics and OIH and allodynia. If a patient
is suspected to be experiencing OIH, carefully consider appropriately decreasing the dose of the current opioid analgesic or opioid rotation (safely switching the patient to a different opioid moiety) [see Dosage and Administration (2.6), Warnings and Precautions (5.12)].

5.6 Life-Threatening Respiratory Depression in Patients with Chronic Pulmonary Disease or in Elderly, Cachectic, or Debilitated Patients

The use of Hydromorphone Hydrochloride Injection in patients with acute or severe bronchial asthma in an unmonitored setting or in the absence of resuscitative equipment is contraindicated.

Patients with Chronic Pulmonary Disease: Hydromorphone Hydrochloride Injection treated patients with significant chronic obstructive pulmonary disease or cor pulmonale, and those with a substantially decreased respiratory reserve, hypoxia, hypercapnia, or pre-existing respiratory depression are at increased risk of decreased respiratory drive including apnea, even at recommended dosages of Hydromorphone Hydrochloride Injection [see Warnings and Precautions (5.2)].

Elderly, Cachectic, or Debilitated Patients: Life-threatening respiratory depression is more likely to occur in elderly, cachectic, or debilitated patients because they may have altered pharmacokinetics or altered clearance compared to younger, healthier patients [see Warnings and Precautions (5.2)].

Monitor such patients closely, particularly when initiating and titrating Hydromorphone Hydrochloride Injection and when Hydromorphone Hydrochloride Injection is given concomitantly with other drugs that depress respiration [see Warnings and Precautions (5.2, 5.3), Drug Interactions (7)]. Alternatively, consider the use of non-opioid analgesics in these patients.

5.7 Adrenal Insufficiency

Cases of adrenal insufficiency have been reported with opioid use, more often following greater than one month of use. Presentation of adrenal insufficiency may include non-specific symptoms and signs including nausea, vomiting, anorexia, fatigue, weakness, dizziness, and low blood pressure. If adrenal insufficiency is suspected, confirm the diagnosis with diagnostic testing as soon as possible. If adrenal insufficiency is diagnosed, treat with physiologic replacement doses of corticosteroids. Wean the patient off of the opioid to allow adrenal function to recover and continue corticosteroid treatment until adrenal function recovers. Other opioids may be tried as some cases reported use of a different opioid without recurrence of adrenal insufficiency. The information available does not identify any particular opioids as being more likely to be associated with adrenal insufficiency.

5.8 Severe Hypotension

Hydromorphone Hydrochloride Injection may cause severe hypotension including orthostatic hypotension and syncope in ambulatory patients. There is increased risk in patients whose ability to maintain blood pressure has already been compromised by a reduced blood volume or concurrent administration of certain CNS depressant drugs (e.g., phenothiazines or general anesthetics) [see Drug Interactions (7)]. Monitor these patients for signs of hypotension after initiating or titrating the dosage of Hydromorphone Hydrochloride Injection. In patients with circulatory shock, Hydromorphone Hydrochloride Injection may cause vasodilation that can further reduce cardiac output and blood pressure. Avoid the use of Hydromorphone Hydrochloride Injection in patients with circulatory shock.

5.9 Risks of Use in Patients with Increased Intracranial Pressure, Brain Tumors, Head Injury, or Impaired Consciousness

In patients who may be susceptible to the intracranial effects of CO2 retention (e.g., those with evidence of increased intracranial pressure or brain tumors), Hydromorphone Hydrochloride Injection may reduce respiratory drive, and the resultant CO2 retention can further increase intracranial pressure. Monitor such patients for signs of sedation and respiratory depression, particularly when initiating therapy with Hydromorphone Hydrochloride Injection.

Opioids may also obscure the clinical course in a patient with a head injury. Avoid the use of Hydromorphone Hydrochloride Injection in patients with impaired consciousness or coma.

5.10 Risks of Use in Patients with Gastrointestinal Conditions

Hydromorphone Hydrochloride Injection is contraindicated in patients with known or suspected gastrointestinal obstruction, including paralytic ileus.

The hydromorphone in Hydromorphone Hydrochloride Injection may cause spasm of the sphincter of Oddi. Opioids may cause increases in serum amylase. Monitor patients with biliary tract disease, including acute pancreatitis, for worsening symptoms.

5.11 Increased Risk of Seizures in Patients with Seizure Disorders

The hydromorphone in Hydromorphone Hydrochloride Injection may increase the frequency of seizures in patients with seizure disorders, and may increase the risk of seizures occurring in other clinical settings associated with seizures. Monitor patients with a history of seizure disorders for worsened seizure control during Hydromorphone Hydrochloride Injection therapy.

5.12 Withdrawal

Avoid the use of mixed agonist/antagonist (e.g., pentazocine, nalbuphine, and butorphanol) or partial agonist (e.g., buprenorphine) analgesics in patients who are receiving a full opioid agonist analgesic, including Hydromorphone Hydrochloride Injection. In these patients, mixed agonist/antagonist and partial agonist analgesics may reduce the analgesic effect and/or precipitate withdrawal symptoms [see Drug Interactions (7)].

When discontinuing Hydromorphone Hydrochloride Injection in a physically-dependent patient, gradually taper the dosage [see Dosage and Administration (2.6)]. Do not abruptly discontinue Hydromorphone Hydrochloride Injection in these patients [see Drug Abuse and Dependence (9.3)].

5.13 Risks of Driving and Operating Machinery

Hydromorphone Hydrochloride Injection may impair the mental or physical abilities needed to perform potentially hazardous activities such as driving a car or operating machinery. Warn patients not to drive or operate dangerous machinery unless they are tolerant to the effects of Hydromorphone Hydrochloride Injection and know how they will react to the medication.

5.14 Increased Risk of Hypotension and Respiratory Depression with Rapid Intravenous Administration

Hydromorphone Hydrochloride Injection may be given intravenously, but the injection should be given very slowly. Rapid intravenous injection of opioid analgesics increases the possibility of side effects such as hypotension and respiratory depression [see Dosage and Administration (2)].

6 ADVERSE REACTIONS

The following serious adverse reactions are described, or described in greater detail, in other sections:

- Addiction, Abuse, and Misuse [see Warnings and Precautions (5.1)]
- Life-Threatening Respiratory Depression [see Warnings and Precautions (5.2)]
- Interactions with Benzodiazepines and Other CNS Depressants [see Warnings and Precautions (5.3)]
- Neonatal Opioid Withdrawal Syndrome [see Warnings and Precautions (5.4)]
- Opioid-Induced Hyperalgesia and Allodynia [see Warnings and Precautions (5.5)]
- Adrenal Insufficiency [see Warnings and Precautions (5.7)]
- Severe Hypotension [see Warnings and Precautions (5.8)]
- Gastrointestinal Adverse Reactions [see Warnings and Precautions (5.10)]
- Seizures [see Warnings and Precautions (5.11)]
- Withdrawal [see Warnings and Precautions (5.12)]

The following adverse reactions associated with the use of hydromorphone were identified in clinical studies or postmarketing reports. Because some of these reactions were reported voluntarily from a population of uncertain size, it is not always possible to reliably estimate their frequency or establish a causal relationship to drug exposure.

Serious adverse reactions associated with Hydromorphone Hydrochloride Injection include respiratory depression and apnea and, to a lesser degree, circulatory depression, respiratory arrest, shock, and cardiac arrest.

The most common adverse effects are lightheadedness, dizziness, sedation, nausea, vomiting, sweating, flushing, dysphoria, euphoria, dry mouth, and pruritus. These effects seem to be more prominent in ambulatory patients and in those not experiencing severe pain.

Less Frequently Observed Adverse Reactions

Cardiac disorders: tachycardia, bradycardia, palpitations

Eye disorders: vision blurred, diplopia, miosis, visual impairment

Gastrointestinal disorders: constipation, ileus, diarrhea, abdominal pain, hypophagia

General disorders and administration site conditions: weakness, feeling abnormal, chills, injection site urticaria, fatigue, injection site reactions, peripheral edema

Hepatobiliary disorders: biliary colic

Immune system disorders: anaphylactic reactions, hypersensitivity reactions

Investigations: hepatic enzymes increased

Metabolism and nutrition disorders: decreased appetite

Musculoskeletal and connective tissue disorders: muscle rigidity

Nervous system disorders: headache, tremor, paraesthesia, nystagmus, increased intracranial pressure, syncope, taste alteration, involuntary muscle contractions, presyncope, convulsion, drowsiness, dyskinesia, hyperalgesia, lethargy, myoclonus, somnolence, intoxication by breastfeeding

Psychiatric disorders: agitation, mood altered, nervousness, anxiety, depression, hallucination, disorientation, insomnia, abnormal dreams

Renal and urinary disorders: urinary retention, urinary hesitation, antidiuretic effects

Reproductive system and breast disorders: erectile dysfunction, pre-eclampsia

Respiratory, thoracic, and mediastinal disorders: bronchospasm, laryngospasm, dyspnea, oropharyngeal swelling

Skin and subcutaneous tissue disorders: injection site pain, urticaria, rash, hyperhidrosis, Impetigo herpetiformis

Vascular disorders: flushing, hypotension, hypertension

Serotonin syndrome: Cases of serotonin syndrome, a potentially life-threatening condition, have been reported during concomitant use of opioids with serotonergic drugs.

Adrenal insufficiency: Cases of adrenal insufficiency have been reported with opioid use, more often following greater than one month of use.

Anaphylaxis: Anaphylaxis has been reported with ingredients contained in Hydromorphone Hydrochloride Injection.

Androgen deficiency: Cases of androgen deficiency have occurred with chronic use of opioids [see Clinical Pharmacology (12.2)].

Hyperalgesia and Allodynia: Cases of hyperalgesia and allodynia have been reported with opioid therapy of any duration [see Warnings and Precautions (5.5)].

Hypoglycemia: Cases of hypoglycemia have been reported in patients taking opioids. Most reports were in patients with at least one predisposing risk factor (e.g., diabetes).

7 DRUG INTERACTIONS

Table 1 includes clinically significant drug interactions with Hydromorphone Hydrochloride Injection.

TABLE 1. Clinically Significant Drug Interactions with Hydromorphone Hydrochloride Injection

Benzodiazepines and other Central Nervous System Depressants (CNS)
Clinical Impact: | Due to additive pharmacologic effect, the concomitant use of benzodiazepines and other CNS depressants, including alcohol, can increase the risk of hypotension, respiratory depression, profound sedation, coma, and death [see Warnings and Precautions (5.3)].
Intervention: | Reserve concomitant prescribing of these drugs for use in patients for whom alternative treatment options are inadequate. Limit dosages and durations to the minimum required. Monitor closely for signs of respiratory depression and sedation[see Warnings and Precautions (5.3)].
Examples: | Benzodiazepines and other sedatives/hypnotics, anxiolytics, tranquilizers, muscle relaxants, general anesthetics, antipsychotics, other opioids, alcohol.
Serotonergic Drugs
Clinical Impact: | The concomitant use of opioids with other drugs that affect the serotonergic neurotransmitter system has resulted in serotonin syndrome.
Intervention: | If concomitant use is warranted, carefully observe the patient, particularly during treatment initiation and dose adjustment. Discontinue Hydromorphone Hydrochloride Injection if serotonin syndrome is suspected.
Examples: | Selective serotonin reuptake inhibitors (SSRIs), serotonin and norepinephrine reuptake inhibitors (SNRIs), tricyclic antidepressants (TCAs), triptans, 5-HT3 receptor antagonists, drugs that effect the serotonin neurotransmitter system (e.g., mirtazapine, trazodone, tramadol), certain muscle relaxants (i.e., cyclobenzaprine, metaxalone), monoamine oxidase (MAO) inhibitors (those intended to treat psychiatric disorders and also others, such as linezolid and intravenous methylene blue).
Monoamine Oxidase Inhibitors (MAOIs)
Clinical Impact: | MAOI interactions with opioids may manifest as serotonin syndrome or opioid toxicity (e.g., respiratory depression, coma) [see Warnings and Precautions (5.2)].
Intervention: | The use of Hydromorphone Hydrochloride Injection is not recommended for patients taking MAOIs or within 14 days of stopping such treatment.; If urgent use of an opioid is necessary, use test doses and frequent titration of small doses to treat pain while closely monitoring blood pressure and signs and symptoms of CNS and respiratory depression.
Examples: | phenelzine, tranylcypromine, linezolid
Mixed Agonist/Antagonist and Partial Agonist Opioid Analgesics
Clinical Impact: | May reduce the analgesic effect of Hydromorphone Hydrochloride Injection and/or precipitate withdrawal syndrome.
Intervention: | Avoid concomitant use.
Examples: | butorphanol, nalbuphine, pentazocine, buprenorphine
Muscle Relaxants
Clinical Impact: | Hydromorphone may enhance the neuromuscular blocking action of skeletal muscle relaxants and produce an increased degree of respiratory depression.
Intervention: | Monitor patients for signs of respiratory depression that may be greater than otherwise expected and decrease the dosage of Hydromorphone Hydrochloride Injection and/or the muscle relaxant as necessary.
Diuretics
Clinical Impact: | Opioids can reduce the efficacy of diuretics by inducing the release of antidiuretic hormone.
Intervention: | Monitor patients for signs of diminished diuresis and/or effects on blood pressure and increase the dosage of the diuretic as needed.
Anticholinergic Drugs
Clinical Impact: | The concomitant use of anticholinergic drugs may increase risk of urinary retention and/or severe constipation, which may lead to paralytic ileus.
Intervention: | Monitor patients for signs of urinary retention or reduced gastric motility when Hydromorphone Hydrochloride Injection is used concomitantly with anticholinergic drugs.

8 USE IN SPECIFIC POPULATIONS

8.1 Pregnancy

Risk Summary

Use of opioid analgesics for an extended period of time during pregnancy may cause neonatal opioid withdrawal syndrome [see Warnings and Precautions (5.4)]. There are reports of neonatal respiratory depression when hydromorphone is used during labor and delivery (see Clinical Considerations). Published studies and postmarketing reports on hydromorphone use during pregnancy are insufficient to inform a drug-associated risk for major birth defects and miscarriage.

In animal reproduction studies, reduced postnatal survival of pups, and decreased body weight were noted following oral treatment of pregnant rats with hydromorphone during gestation and through lactation at doses 0.8 times the human daily dose of 24 mg/day (HDD), respectively. In published studies, neural tube defects were noted following subcutaneous injection of hydromorphone to pregnant hamsters at doses 6.4 times the HDD and soft tissue and skeletal abnormalities were noted following subcutaneous continuous infusion of 3 times the HDD to pregnant mice. No malformations were noted at 4 or 40.5 times the HDD in pregnant rats or rabbits, respectively (see Data). Based on human and animal data, advise pregnant women of the potential risk to a fetus.

The background risk of major birth defects and miscarriage for the indicated population is unknown. All pregnancies have a background risk of birth defect, loss, or other adverse outcomes. In the U.S. general population, the estimated background risk of major birth defects and miscarriage in clinically recognized pregnancies is 2 to 4% and 15 to 20%, respectively.

Clinical Considerations

Fetal/Neonatal Adverse Reactions

Use of opioid analgesics for an extended period of time during pregnancy for medical or nonmedical purposes can result in physical dependence in the neonate and neonatal opioid withdrawal syndrome shortly after birth.

Neonatal opioid withdrawal syndrome presents as irritability, hyperactivity and abnormal sleep pattern, high pitched cry, tremor, vomiting, diarrhea, and failure to gain weight. The onset, duration, and severity of neonatal opioid withdrawal syndrome vary based on the specific opioid used, duration of use, timing and amount of last maternal use, and rate of elimination of the drug by the newborn. Observe newborns for symptoms of neonatal opioid withdrawal syndrome and manage accordingly [see Warnings and Precautions (5.4)].

Labor or Delivery

Opioids cross the placenta and may produce respiratory depression and psycho-physiologic effects in neonates. An opioid antagonist, such as naloxone, must be available for reversal of opioid-induced respiratory depression in the neonate. Hydromorphone Hydrochloride Injection is not recommended for use in pregnant women during or immediately prior to labor, when other analgesic techniques are more appropriate. Opioid analgesics, including Hydromorphone Hydrochloride Injection, can prolong labor through actions which temporarily reduce the strength, duration, and frequency of uterine contractions. However, this effect is not consistent and may be offset by an increased rate of cervical dilation, which tends to shorten labor. Monitor neonates exposed to opioid analgesics during labor for signs of excess sedation and respiratory depression.

Data

Animal Data

Pregnant rats were treated with hydromorphone hydrochloride from Gestation Day 6 to 17 via oral gavage doses of 1, 5, or 10 mg/kg/day (0.4, 2, or 4 times the HDD of 24 mg based on body surface area, respectively). Maternal toxicity was noted in all treatment groups (reduced food consumption and body weights in the two highest dose groups). There was no evidence of malformations or embryotoxicity reported.

Pregnant rabbits were treated with hydromorphone hydrochloride from Gestation Day 7 to 19 via oral gavage doses of 10, 25, or 50 mg/kg/day (8.1, 20.3, or 40.5 times the HDD of 24 mg based on body surface area, respectively). Maternal toxicity was noted in the two highest dose groups (reduced food consumption and body weights). There was no evidence of malformations or embryotoxicity reported.

In a published study, neural tube defects (exencephaly and cranioschisis) were noted following subcutaneous administration of hydromorphone hydrochloride (19 to 258 mg/kg) on Gestation Day 8 to pregnant hamsters (6.4 to 87.2 times the HDD of 24 mg/day based on body surface area). The findings cannot be clearly attributed to maternal toxicity. No neural tube defects were noted at 14 mg/kg (4.7 times the human daily dose of 24 mg/day).

In a published study, CF-1 mice were treated subcutaneously with continuous infusion of 7.5, 15, or 30 mg/kg/day hydromorphone hydrochloride (1.5, 3, or 6.1 times the human daily dose of 24 mg based on body surface area) via implanted osmotic pumps during organogenesis (Gestation Days 7 to 10). Soft tissue malformations (cryptorchidism, cleft palate, malformed ventricles and retina), and skeletal variations (split supraoccipital, checkerboard and split sternebrae, delayed ossification of the paws and ectopic ossification sites) were observed at doses 3 times the human dose of 24 mg/day based on body surface area. The findings cannot be clearly attributed to maternal toxicity.

Increased pup mortality and decreased pup body weights were noted at 0.8 and 2 times the human daily dose of 24 mg in a study in which pregnant rats were treated with hydromorphone hydrochloride from Gestation Day 7 to Lactation Day 20 via oral gavage doses of 0, 0.5, 2, or 5 mg/kg/day (0.2, 0.8, or 2 times the HDD of 24 mg based on body surface area, respectively). Maternal toxicity (decreased food consumption and body weight gain) was also noted at the two highest doses tested.

8.2 Lactation

Risk Summary

Hydromorphone hydrochloride is transferred into human milk. There are reports of excessive sedation and respiratory depression in breastfed infants exposed to hydromorphone hydrochloride. There is no information on the effects of hydromorphone hydrochloride on milk production.

The developmental and health benefits of breastfeeding should be considered along with the mother’s clinical need for Hydromorphone Hydrochloride Injection and any potential adverse effects on the breastfed infant from Hydromorphone Hydrochloride Injection or from the underlying maternal condition.

Clinical Considerations

Monitor infants exposed to Hydromorphone Hydrochloride Injection through breast milk for excess sedation and respiratory depression. Withdrawal symptoms can occur in breastfed infants when maternal administration of hydromorphone is stopped, or when breast-feeding is stopped.

8.3 Females and Males of Reproductive Potential

Infertility

Chronic use of opioids may cause reduced fertility in females and males of reproductive potential. It is not known whether these effects on fertility are reversible [see Adverse Reactions (6), Clinical Pharmacology (12.2), Nonclinical Toxicology (13.1)].

8.4 Pediatric Use

The safety and effectiveness of Hydromorphone Hydrochloride Injection in pediatric patients has not been established.

8.5 Geriatric Use

Elderly patients (aged 65 years or older) may have increased sensitivity to hydromorphone. In general, use caution when selecting a dosage for an elderly patient, usually starting at the low end of the dosing range, reflecting the greater frequency of decreased hepatic, renal, or cardiac function and of concomitant disease or other drug therapy.

Respiratory depression is the chief risk for elderly patients treated with opioids, and has occurred after large initial doses were administered to patients who were not opioid-tolerant or when opioids were co-administered with other agents that depress respiration. Titrate the dosage of Hydromorphone Hydrochloride Injection slowly in geriatric patients and monitor closely for signs of central nervous system and respiratory depression [see Warnings and Precautions (5.6)].

Hydromorphone is known to be substantially excreted by the kidney, and the risk of adverse reactions to this drug may be greater in patients with impaired renal function. Because elderly patients are more likely to have decreased renal function, care should be taken in dose selection, and it may be useful to monitor renal function.

8.6 Hepatic Impairment

The pharmacokinetics of hydromorphone are affected by hepatic impairment. Due to increased exposure of hydromorphone, patients with moderate hepatic impairment should be started at one-fourth to one-half the recommended starting dose depending on the degree of hepatic dysfunction and closely monitored during dose titration. The pharmacokinetics of hydromorphone in patients with severe hepatic impairment has not been studied. A further increase in Cmax and AUC of hydromorphone in this group is expected and should be taken into consideration when selecting a starting dose [see Clinical Pharmacology (12.3)].

8.7 Renal Impairment

The pharmacokinetics of hydromorphone are affected by renal impairment. Start patients with renal impairment on one-fourth to one-half the usual starting dose depending on the degree of impairment. Patients with renal impairment should be closely monitored during dose titration [see Clinical Pharmacology (12.3)].

9 DRUG ABUSE AND DEPENDENCE

9.1 Controlled Substance

Hydromorphone Hydrochloride Injection contains hydromorphone, which is a Schedule II controlled substance.

9.2 Abuse

Hydromorphone Hydrochloride Injection contains hydromorphone hydrochloride, a substance with a high potential for misuse and abuse, which can lead to the development of substance use disorder, including addiction [see Warnings and Precautions (5.1)].

Misuse is the intentional use, for therapeutic purposes, of a drug by an individual in a way other than prescribed by a healthcare provider or for whom it was not prescribed.

Abuse is the intentional, non-therapeutic use of a drug, even once, for its desirable psychological or physiological effects.

Drug addiction is a cluster of behavioral, cognitive, and physiological phenomena that may include a strong desire to take the drug, difficulties in controlling drug use (e.g., continuing drug use despite harmful consequences, giving a higher priority to drug use than other activities and obligations), and possible tolerance or physical dependence.

Misuse and abuse of Hydromorphone Hydrochloride Injection increases risk of overdose, which may lead to central nervous system and respiratory depression, hypotension, seizures, and death. The risk is increased with concurrent abuse of Hydromorphone Hydrochloride Injection with alcohol and/or other CNS depressants. Abuse of and addiction to opioids in some individuals may not be accompanied by concurrent tolerance and symptoms of physical dependence. In addition, abuse of opioids can occur in the absence of addiction.

All patients treated with opioids require careful and frequent reevaluation for signs of misuse, abuse, and addiction, because use of opioid analgesic products carries the risk of addiction even under appropriate medical use. Patients at high risk of Hydromorphone Hydrochloride Injection abuse include those with a history of prolonged use of any opioid, including products containing hydromorphone, those with a history of drug or alcohol abuse, or those who use Hydromorphone Hydrochloride Injection in combination with other abused drugs.

“Drug-seeking” behavior is very common in persons with substance use disorders. Drug-seeking tactics include emergency calls or visits near the end of office hours, refusal to undergo appropriate examination, testing, or referral, repeated “loss” of prescriptions, tampering with prescriptions, and reluctance to provide prior medical records or contact information for other treating healthcare provider(s). “Doctor shopping” (visiting multiple prescribers to obtain additional prescriptions) is common among people who abuse drugs and people with substance use disorder. Preoccupation with achieving adequate pain relief can be appropriate behavior in a patient with inadequate pain control.

Hydromorphone Hydrochloride Injection, like other opioids, can be diverted for nonmedical use into illicit channels of distribution. Careful record-keeping of prescribing information, including quantity, frequency, and renewal requests, as required by state and federal law, is strongly advised.

Proper assessment of the patient, proper prescribing practices, periodic reevaluation of therapy, and proper dispensing and storage are appropriate measures that help to limit abuse of opioid drugs.

Risks Specific to Abuse of Hydromorphone Hydrochloride Injection

Abuse of Hydromorphone Hydrochloride Injection poses a risk of overdose and death. The risk is increased with concurrent use of Hydromorphone Hydrochloride Injection with alcohol and/or other CNS depressants.

Parenteral drug abuse is commonly associated with transmission of infectious diseases such as hepatitis and HIV.

9.3 Dependence

Both tolerance and physical dependence can develop during chronic opioid therapy.

Tolerance is a physiological state characterized by a reduced response to a drug after repeated administration (i.e., a higher dose of a drug is required to produce the same effect that was once obtained at a lower dose).

Physical dependence is a state that develops as a result of a physiological adaptation in response to repeated drug use, manifested by withdrawal signs and symptoms after abrupt discontinuation or a significant dose reduction of a drug.

Withdrawal may be precipitated through the administration of drugs with opioid antagonist activity (e.g., naloxone), mixed agonist/antagonist analgesics (e.g., pentazocine, butorphanol, nalbuphine), or partial agonists (e.g., buprenorphine). Physical dependence may not occur to a clinically significant degree until after several days to weeks of continued use.

Hydromorphone Hydrochloride Injection should not be abruptly discontinued in a physically-dependent patient [see Dosage and Administration (2.6)]. If Hydromorphone Hydrochloride Injection is abruptly discontinued in a physically-dependent patient, a withdrawal syndrome may occur, typically characterized by restlessness, lacrimation, rhinorrhea, perspiration, chills, myalgia, and mydriasis. Other signs and symptoms also may develop, including irritability, anxiety, backache, joint pain, weakness, abdominal cramps, insomnia, nausea, anorexia, vomiting, diarrhea, or increased blood pressure, respiratory rate, or heart rate.

Infants born to mothers physically dependent on opioids will also be physically dependent and may exhibit respiratory difficulties and withdrawal signs [see Use in Specific Populations (8.1)].

10 OVERDOSAGE

Clinical Presentation

Acute overdose with hydromorphone can be manifested by respiratory depression, somnolence progressing to stupor or coma, skeletal muscle flaccidity, cold and clammy skin, constricted pupils, and, in some cases, pulmonary edema, bradycardia, hypotension, hypoglycemia, partial or complete airway obstruction, atypical snoring, and death. Marked mydriasis, rather than miosis, may be seen with hypoxia in overdose situations [see Clinical Pharmacology (12.2)].

Treatment of Overdose

In case of overdose, priorities are the reestablishment of a patent airway and protected airway and institution of assisted or controlled ventilation, if needed. Employ other supportive measures (including oxygen and vasopressors) in the management of circulatory shock and pulmonary edema as indicated. Cardiac arrest or arrhythmias will require advanced life-support measures.

Opioid antagonists, such as naloxone, are specific antidotes to respiratory depression resulting from opioid overdose. For clinically significant respiratory or circulatory depression secondary to hydromorphone overdose, administer an opioid antagonist.

Because the duration of opioid reversal is expected to be less than the duration of hydromorphone in Hydromorphone Hydrochloride Injection, carefully monitor the patient until spontaneous respiration is reliably reestablished. If the response to an opioid antagonist is suboptimal or only brief in nature, administer additional antagonist as directed by the product’s prescribing information.

In an individual physically dependent on opioids, administration of the recommended usual dosage of the antagonist will precipitate an acute withdrawal syndrome. The severity of the withdrawal symptoms experienced will depend on the degree of physical dependence and the dose of the antagonist administered. If a decision is made to treat serious respiratory depression in the physically dependent patient, administration of the antagonist should be initiated with care and by titration with smaller than usual doses of the antagonist.

11 DESCRIPTION

Hydromorphone Hydrochloride is an opioid agonist.

The chemical name of hydromorphone hydrochloride is 4,5α-epoxy-3-hydroxy-17-methylmorphinan-6-one hydrochloride. The molecular weight is 321.80. Its molecular formula is C17H19NO3·HCl, and it has the following chemical structure:

Hydromorphone hydrochloride is a white to off-white powder that is freely soluble in water, very slightly soluble in ethanol (96%), and practically insoluble in methylene chloride.

Hydromorphone Hydrochloride Injection 40 mg/20 mL is available as a sterile, clear, colorless aqueous solution in a multiple-dose clear glass vial, for slow intravenous, subcutaneous, or intramuscular administration. Each 1 mL contains 2 mg of hydromorphone hydrochloride (equivalent to 1.8 mg hydromorphone). The inactive ingredients include edetate disodium dihydrate (0.5 mg/mL), methylparaben (1.8 mg/mL), and propylparaben (0.2 mg/mL). Hydrochloric acid and sodium hydroxide are added to adjust the pH between 3.5 and 5.5.

12 CLINICAL PHARMACOLOGY

12.1 Mechanism of Action

Hydromorphone is a full opioid agonist and is relatively selective for the mu-opioid receptor, although it can bind to other opioid receptors at higher doses. The principal therapeutic action of hydromorphone is analgesia. Like all full opioid agonists, there is no ceiling effect for analgesia with morphine. Clinically, dosage is titrated to provide adequate analgesia and may be limited by adverse reactions, including respiratory and CNS depression.

The precise mechanism of the analgesic action is unknown. However, specific CNS opioid receptors for endogenous compounds with opioid-like activity have been identified throughout the brain and spinal cord and are thought to play a role in the analgesic effects of this drug.

12.2 Pharmacodynamics

Effects on the Central Nervous System

Hydromorphone produces respiratory depression by direct effect on brain stem respiratory centers. The respiratory depression involves a reduction in the responsiveness of the brain stem respiratory centers to both increases in carbon dioxide tension and electrical stimulation.

Hydromorphone causes miosis, even in total darkness. Pinpoint pupils are a sign of opioid overdose but are not pathognomonic (e.g., pontine lesions of hemorrhagic or ischemic origin may produce similar findings). Marked mydriasis rather than miosis may be seen due to hypoxia in overdose situations.

Effects on the Gastrointestinal Tract and Other Smooth Muscle

Hydromorphone causes a reduction in motility associated with an increase in smooth muscle tone in the antrum of the stomach and duodenum. Digestion of food in the small intestine is delayed and propulsive contractions are decreased. Propulsive peristaltic waves in the colon are decreased, while tone may be increased to the point of spasm, resulting in constipation. Other opioid-induced effects may include a reduction in biliary and pancreatic secretions, spasm of sphincter of Oddi, and transient elevations in serum amylase.

Effects on the Cardiovascular System

Hydromorphone produces peripheral vasodilation which may result in orthostatic hypotension or syncope, manifestations of histamine release and/or peripheral vasodilation may include pruritus, flushing, red eyes, and sweating and/or orthostatic hypotension.

Effects on the Endocrine System

Opioids inhibit the secretion of adrenocorticotropic hormone (ACTH), cortisol, and luteinizing hormone (LH) in humans [see Adverse Reactions (6)]. They also stimulate prolactin, growth hormone (GH) secretion, and pancreatic secretion of insulin and glucagon.

Use of opioids for an extended period of time may influence the hypothalamic-pituitary-gonadal axis, leading to androgen deficiency that may manifest as low libido, impotence, erectile dysfunction, amenorrhea, or infertility. The causal role of opioids in the clinical syndrome of hypogonadism is unknown because the various medical, physical, lifestyle, and psychological stressors that may influence gonadal hormone levels have not been adequately controlled for in studies conducted to date [see Adverse Reactions (6)].

Effects on the Immune System

Opioids have been shown to have a variety of effects on components of the immune system in in vitro and animal models. The clinical significance of these findings is unknown. Overall, the effects of opioids appear to be modestly immunosuppressive.

Concentration–Efficacy Relationships

The minimum effective analgesic concentration will vary widely among patients, especially among patients who have been previously treated with opioid agonists. The minimum effective analgesic concentration of hydromorphone for any individual patient may increase over time due to an increase in pain, the development of a new pain syndrome, and/or the development of analgesic tolerance [see Dosage and Administration (2.1, 2.2)].

Concentration–Adverse Reaction Relationships

There is a relationship between increasing hydromorphone plasma concentration and increasing frequency of dose-related opioid adverse reactions such as nausea, vomiting, CNS effects, and respiratory depression. In opioid-tolerant patients, the situation may be altered by the development of tolerance to opioid-related adverse reactions [see Dosage and Administration (2.1, 2.2)].

12.3 Pharmacokinetics

Distribution

At therapeutic plasma levels, hydromorphone is approximately 8-19% bound to plasma proteins. After an intravenous bolus dose, the steady state of volume of distribution [mean (%CV)] is 302.9 (32%) liters.

Elimination

The systemic clearance is approximately 1.96 (20%) liters/minute. The terminal elimination half-life of hydromorphone after an intravenous dose is about 2.3 hours.

Metabolism

Hydromorphone is extensively metabolized via glucuronidation in the liver, with greater than 95% of the dose metabolized to hydromorphone-3-glucuronide along with minor amounts of 6-hydroxy reduction metabolites.

Excretion

Only a small amount of the hydromorphone dose is excreted unchanged in the urine. Most of the dose is excreted as hydromorphone-3-glucuronide along with minor amounts of 6-hydroxy reduction metabolites.

Special Populations

Hepatic Impairment

After oral administration of hydromorphone at a single 4 mg dose (2 mg hydromorphone immediate-release tablets), mean exposure to hydromorphone (Cmax and AUC∞) is increased 4-fold in patients with moderate (Child-Pugh Group B) hepatic impairment compared with subjects with normal hepatic function. Patients with moderate hepatic impairment should be started at one-fourth to one-half the recommended starting dose and closely monitored during dose titration. The pharmacokinetics of hydromorphone in patients with severe hepatic impairment has not been studied. A further increase in Cmax and AUC of hydromorphone in this group is expected and should be taken into consideration when selecting a starting dose [see Use in Specific Populations (8.6)].

Renal Impairment

The pharmacokinetics of hydromorphone following an oral administration of hydromorphone at a single 4 mg dose (2 mg hydromorphone immediate-release tablets) are affected by renal impairment. Mean exposure to hydromorphone (Cmax and AUC0-∞) is increased by 2-fold in patients with moderate (CLcr = 40 - 60 mL/min) renal impairment and increased by 4-fold in patients with severe (CLcr< 30 mL/min) renal impairment compared with normal subjects (CLcr> 80 mL/min). In addition, in patients with severe renal impairment, hydromorphone appeared to be more slowly eliminated with a longer terminal elimination half-life (40 hr) compared to patients with normal renal function (15 hr). Start patients with renal impairment on one-fourth to one-half the usual starting dose depending on the degree of impairment. Patients with renal impairment should be closely monitored during dose titration [see Use in Specific Populations (8.7)].

Geriatric Population

In the geriatric population, age has no effect on the pharmacokinetics of hydromorphone.

Sex

Sex has little effect on the pharmacokinetics of hydromorphone. Females appear to have a higher Cmax (25%) than males with comparable AUC0-24 values. The difference observed in Cmax may not be clinically relevant.

13 NONCLINICAL TOXICOLOGY

13.1 Carcinogenesis, Mutagenesis, Impairment of Fertility

Carcinogenesis

Long term studies in animals to evaluate the carcinogenic potential of hydromorphone have not been conducted.

Mutagenesis

Hydromorphone was positive in the mouse lymphoma assay in the presence of metabolic activation, but was negative in the mouse lymphoma assay in the absence of metabolic activation. Hydromorphone was not mutagenic in the in vitro bacterial reverse mutation assay (Ames assay). Hydromorphone was not clastogenic in either the in vitro human lymphocyte chromosome aberration assay or the in vivo mouse micronucleus assay.

Impairment of Fertility

Reduced implantation sites and viable fetuses were noted at 2.1 times the human daily dose of 32 mg/day in a study in which female rats were treated orally with 1.75, 3.5, or 7 mg/kg/day hydromorphone hydrochloride (0.5, 1.1, or 2.1 times a human daily dose of 24 mg/day (HDD) based on body surface area) beginning 14 days prior to mating through Gestation Day 7 and male rats were treated with the same hydromorphone hydrochloride doses beginning 28 days prior to and throughout mating.

16 HOW SUPPLIED/STORAGE AND HANDLING

Hydromorphone Hydrochloride Injection is a clear, colorless, sterile, aqueous solution available in multi-dose clear glass vial containing 40 mg/20 mL (2 mg/mL). It is supplied in the following packaging configuration:

- Carton containing 1 multi-dose vial: NDC 0641-6254-01

Store at 20°C to 25°C (68°F to 77°F); excursions permitted to 15°C to 30°C (59°F to 86°F) [See USP Controlled Room Temperature]. Protect from light.

17 PATIENT COUNSELING INFORMATION

Addiction, Abuse, and Misuse

Inform patients that the use of Hydromorphone Hydrochloride Injection, even when taken as recommended, can result in addiction, abuse, and misuse, which can lead to overdose and death [see Warnings and Precautions (5.1)].

Life-Threatening Respiratory Depression

Inform patients of the risk of life-threatening respiratory depression, including information that the risk is greatest when starting Hydromorphone Hydrochloride Injection or when the dosage is increased, and that it can occur even at recommended dosages [see Warnings and Precautions (5.2)].

Hyperalgesia and Allodynia

Advise patients to inform their healthcare provider if they experience symptoms of hyperalgesia, including worsening pain, increased sensitivity to pain, or new pain [see Warnings and Precautions (5.5), Adverse Reactions (6)].

Serotonin Syndrome

Inform patients that opioids could cause a rare but potentially life-threatening condition called serotonin syndrome resulting from concomitant administration of serotonergic drugs. Warn patients of the symptoms of serotonin syndrome and to seek medical attention right away if symptoms develop after discharge from the hospital. Instruct patients to inform their healthcare providers if they are taking, or plan to take serotonergic medications [see Drug Interactions (7)].

Constipation

Advise patients of the potential for severe constipation, including management instructions and when to seek medical attention [see Adverse Reactions (6)].

Pregnancy

Neonatal Opioid Withdrawal Syndrome

Inform female patients of reproductive potential that use of hydromorphone for an extended period of time during pregnancy can result in neonatal opioid withdrawal syndrome, which may be life threatening if not recognized and treated [see Warnings and Precautions (5.3), Use in Specific Populations (8.1)].

Embryo-Fetal Toxicity

Inform female patients of reproductive potential that hydromorphone may cause fetal harm and to inform their prescriber of a known or suspected pregnancy [see Use in Specific Populations (8.1)].

Lactation

Advise nursing mothers to monitor infants for increased sleepiness (more than usual), breathing difficulties, or limpness. Instruct nursing mothers to seek immediate medical care if they notice these signs [see Use in Specific Populations (8.2)].

Infertility

Inform patients that use of opioids for an extended period of time may cause reduced fertility. It is not known whether these effects on fertility are reversible [see Use in Specific Populations (8.3)].

To report SUSPECTED ADVERSE REACTIONS, contact Hikma Pharmaceuticals USA Inc. at 1-877-845-0689, or the FDA at 1-800-FDA-1088 or www.fda.gov/medwatch.

Manufactured by:

Hikma Pharmaceuticals USA Inc.

Berkeley Heights, NJ 07922

462-965-00

PRINCIPAL DISPLAY PANEL

NDC 0641-6254-01

Rx Only

HYDROmorphone HCI Injection CII

40 mg per 20 mL

(2 mg/mL)

For Subcutaneous, Intramuscular, or slow Intravenous use

20 mL Multiple-Dose Vial

NDC 0641-6254-01

Rx Only

HYDROmorphone HCI Injection CII

40 mg per 20 mL

(2 mg/mL)

For Subcutaneous, Intramuscular, or slow Intravenous use

1 x 20 mL Multiple-Dose Vial